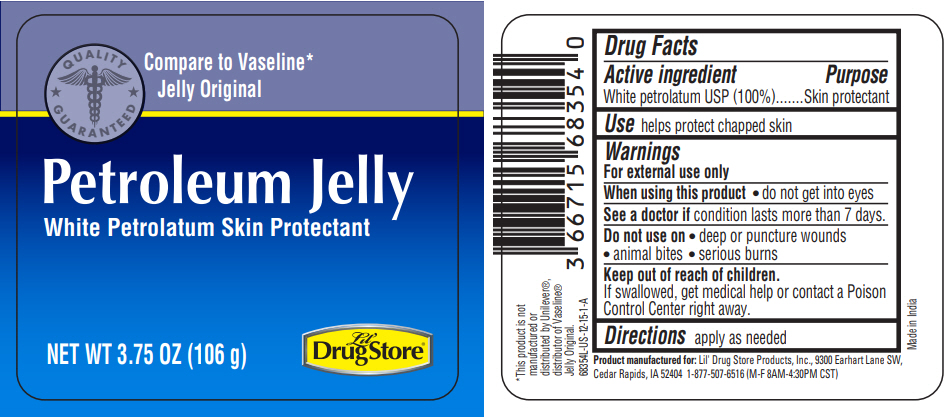 DRUG LABEL: Lil Drug Store Petroleum Jelly
NDC: 66715-6835 | Form: JELLY
Manufacturer: Lil Drug Store Products, Inc
Category: otc | Type: HUMAN OTC DRUG LABEL
Date: 20241125

ACTIVE INGREDIENTS: PETROLATUM 1 g/1 g

Lil' Drug Store® Petroleum Jelly

Drug Facts

Active ingredient

White petrolatum USP (100%)

Purpose

Skin protectant

Use

helps protect chapped skin

Warnings

For external use only

When using this product

- do not get into eyes

See a doctor if condition lasts more than 7 days.

Do not use on

- deep or puncture wounds
- animal bites
- serious burns

Keep out of reach of children.

If swallowed, get medical help or contact a Poison Control Center right away.

Directions

apply as needed

PRINCIPAL DISPLAY PANEL - 106 g Jar Label

QUALITY
⋆ GUARANTEED ⋆

Compare to Vaseline*
Jelly Original

Petroleum Jelly
White Petrolatum Skin Protectant

NET WT 3.75 OZ (106 g)

Lil'
Drug Store®